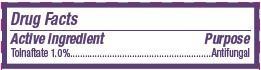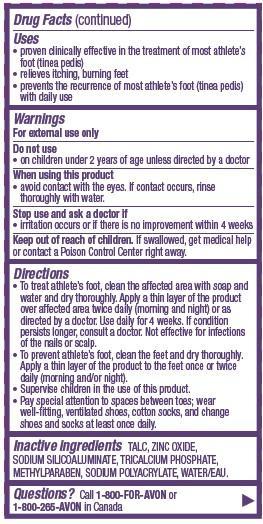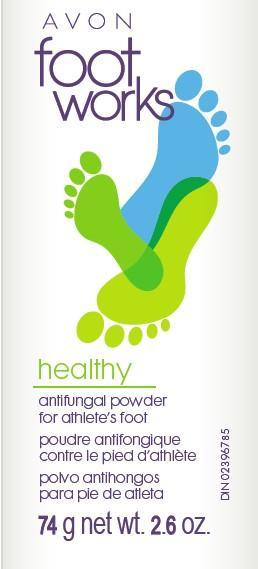 DRUG LABEL: Foot Works Healthy
NDC: 10096-0303 | Form: POWDER
Manufacturer: New Avon LLC
Category: otc | Type: HUMAN OTC DRUG LABEL
Date: 20190101

ACTIVE INGREDIENTS: TOLNAFTATE	 10 mg/1 g
INACTIVE INGREDIENTS: WATER

Footworks Antifungal Powder

Active ingredient
Tolnaftate 1.0%.........................

Purpose
.......................Antifungal

Uses
• proven clinically effective in the treatment of most athlete’s foot (tinea pedis)
• relieves itching, burning feet
• prevents the recurrence of most athlete’s foot (tinea pedis) with daily use

Warnings
For external use only

Do not use
• on children under 2 years of age unless directed by a doctor

When using this product
• avoid contact with the eyes. If contact occurs, rinse thoroughly with water.

Stop use and ask a doctor if
• irritation occurs or if there is no improvement within 4 weeks

Keep out of reach of children. If swallowed, get medical help or contact a Poison Control Center right away.

Directions
• To treat athlete’s foot, clean the affected area with soap and water and dry thoroughly. Apply a thin layer of the product over affected area twice daily (morning and night) or as directed by a doctor. Use daily for 4 weeks. If condition persists longer, consult a doctor. Not effective for infections of the nails or scalp.

• To prevent athlete’s foot, clean the feet and dry thoroughly. Apply a thin layer of the product to the feet once or twice daily (morning and/or night).
• Supervise children in the use of this product.
• Pay special attention to spaces between toes; wear well-fitting, ventilated shoes, cotton socks, and change shoes and socks at least once daily.

Inactive ingredients
TALC, ZINC OXIDE, SODIUM SILICOALUMINATE, TRICALCIUM PHOSPHATE, METHYLPARABEN, SODIUM POLYACRYLATE, WATER/EAU.

QUESTIONS

QUESTIONS? Call 1-800-FOR-AVON or 1-800-265-AVON in Canada